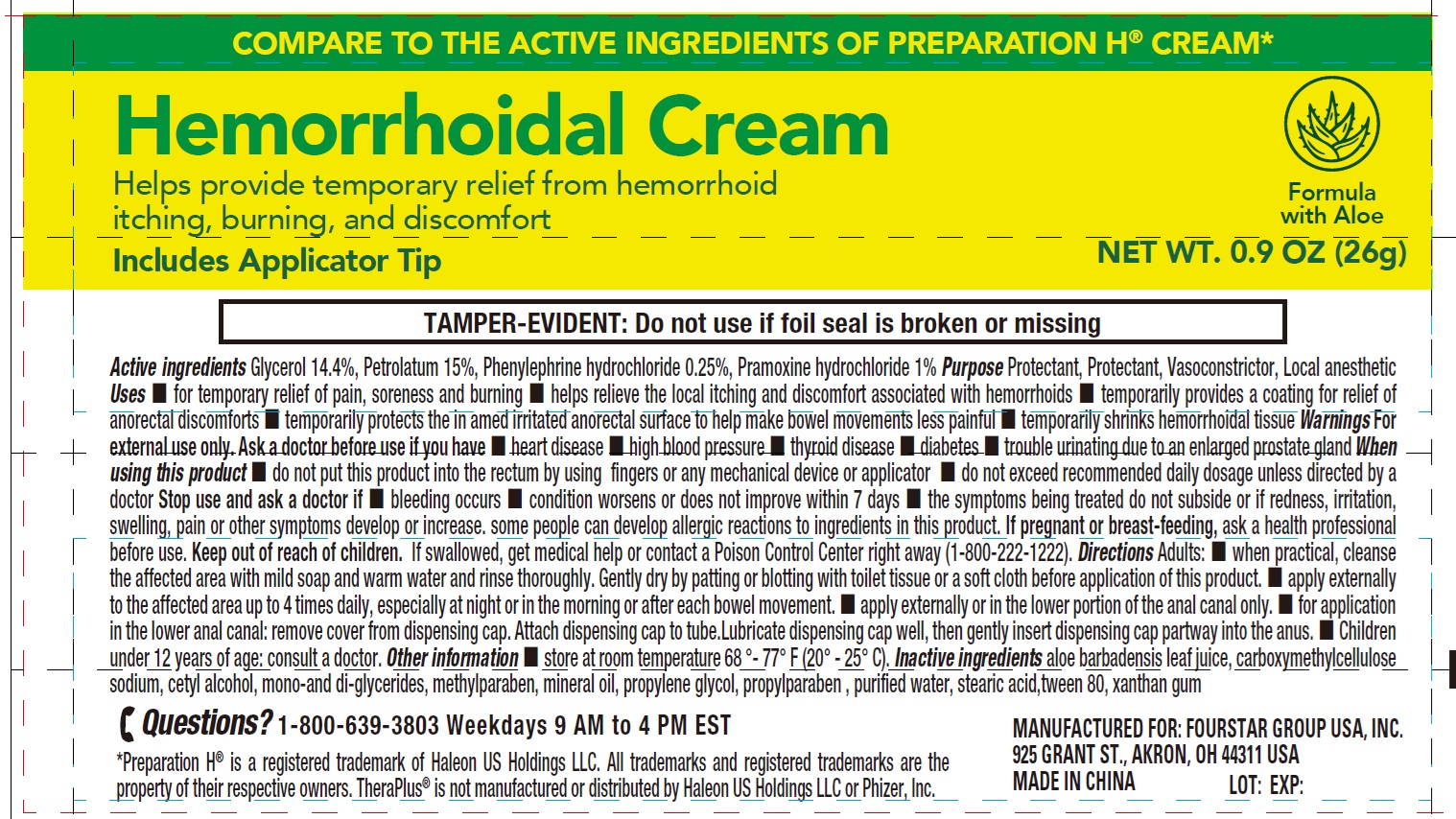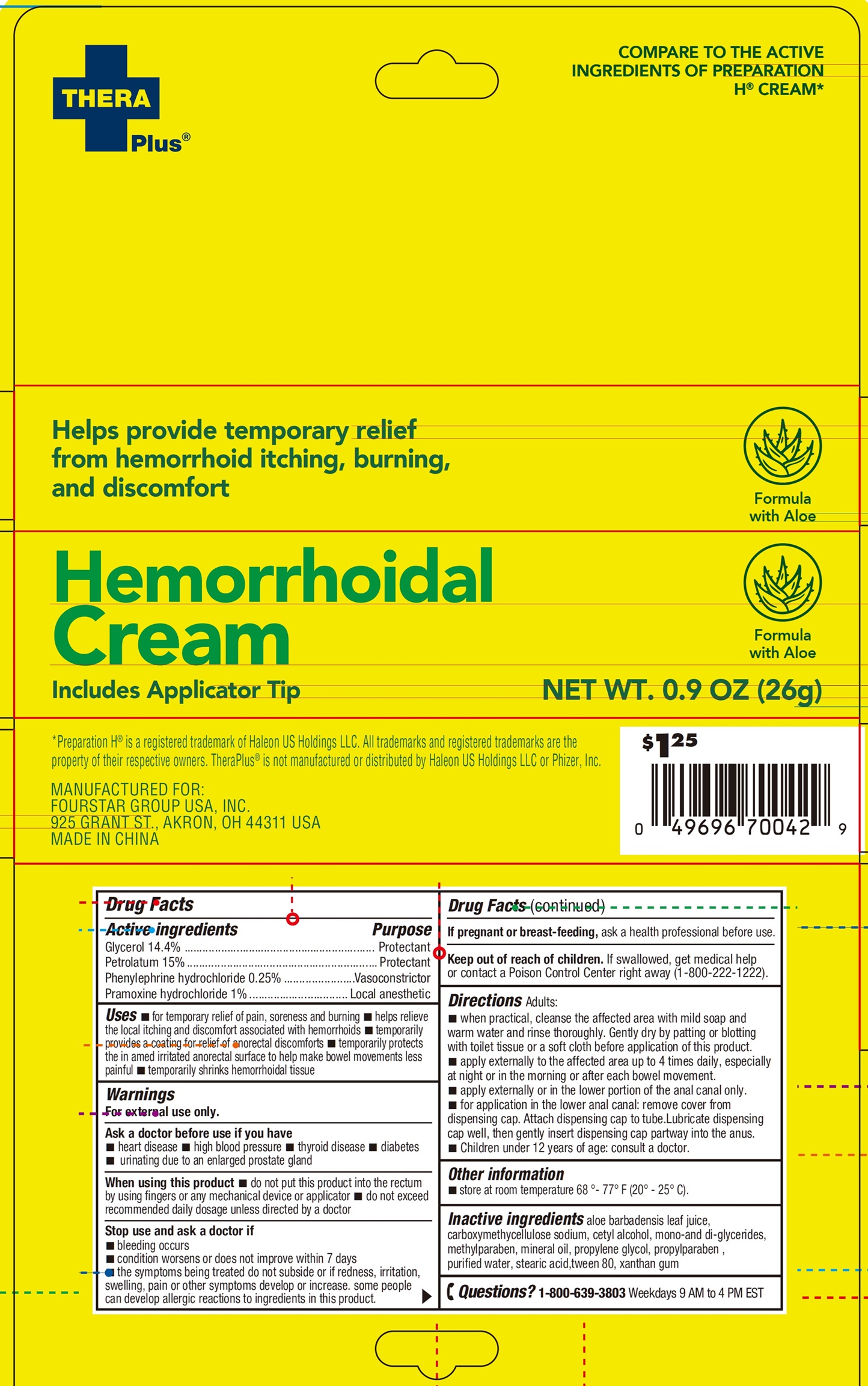 DRUG LABEL: Thera Plus Hemorrhoidal
NDC: 80684-141 | Form: CREAM
Manufacturer: FOURSTAR GROUP USA, INC.
Category: otc | Type: HUMAN OTC DRUG LABEL
Date: 20250304

ACTIVE INGREDIENTS: GLYCERIN 144 mg/1 g; PETROLATUM 150 mg/1 g; PHENYLEPHRINE HYDROCHLORIDE 2.5 mg/1 g; PRAMOXINE HYDROCHLORIDE 10 mg/1 g
INACTIVE INGREDIENTS: ALOE VERA LEAF; CARBOXYMETHYLCELLULOSE SODIUM, UNSPECIFIED; CETYL ALCOHOL; METHYLPARABEN; MINERAL OIL; PROPYLENE GLYCOL; PROPYLPARABEN; WATER; STEARIC ACID; POLYSORBATE 80; XANTHAN GUM

Thera Plus Hemorrhoidal Cream

Active ingredients

Glycerol 14.4%
Petrolatum 15%
Phenylephrine hydrochloride 0.25%
Pramoxine hydrochloride 1%

Purpose

Protectant

Vasoconstrictor

Local anesthetic

Uses

- for temporary relief of pain, soreness and burning
- helps relieve the local itching and discomfort associated with hemorrhoids
- temporarily provides a coating for relief of anorectal discomforts
- temporarily protects the in amed irritated anorectal surface to help make bowel movements less painful
- temporarily shrinks hemorrhoidal tissue

Warnings

For external use only.

Ask a doctor before use if you have

- heart disease
- high blood pressure
- thyroid disease
- diabetes
- urinating due to an enlarged prostate gland

When using this product

- do not put this product into the rectum by using fingers or any mechanical device or applicator
- do not exceed recommended daily dosage unless directed by a doctor

Stop use and ask a doctor if

- bleeding occurs
- condition worsens or does not improve within 7 days
- the symptoms being treated do not subside or if redness, irritation, swelling, pain or other symptoms develop or increase. some people can develop allergic reactions to ingredients in this product.

If pregnant or breast-feeding,

ask a health professional before use.

Keep out of reach of children.

If swallowed, get medical help or contact a Poison Control Center right away (1-800-222-1222).

Directions

Adults:

- when practical, cleanse the affected area with mild soap and warm water and rinse thoroughly. Gently dry by patting or blotting with toilet tissue or a soft cloth before application of this product.
- apply externally to the affected area up to 4 times daily, especially at night or in the morning or after each bowel movement.
- apply externally or in the lower portion of the anal canal only.
- for application in the lower anal canal: remove cover from dispensing cap. Attach dispensing cap to tube.Lubricate dispensing cap well, then gently insert dispensing cap partway into the anus.
- Children under 12 years of age: consult a doctor.

Other information

- store at room temperature 68 °- 77° F (20° - 25° C).

Inactive ingredients

aloe barbadensis leaf juice, carboxymethycellulose sodium, cetyl alcohol, mono-and di-glycerides, methylparaben, mineral oil, propylene glycol, propylparaben , purified water, stearic acid,tween 80, xanthan gum

Questions?

1-800-639-3803Weekdays 9 AM to 4 PM EST